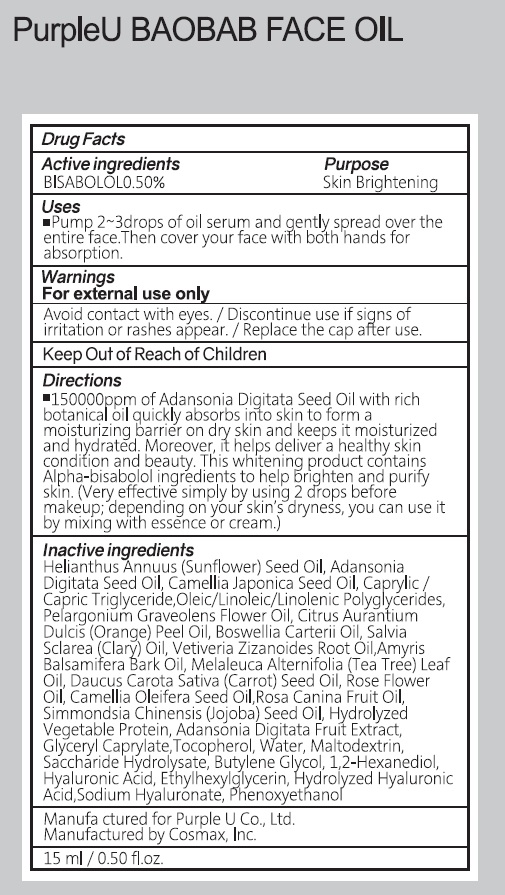 DRUG LABEL: PurpleU BAOBAB FACE
NDC: 71732-020 | Form: OIL
Manufacturer: Recipe Co., Ltd.
Category: otc | Type: HUMAN OTC DRUG LABEL
Date: 20171208

ACTIVE INGREDIENTS: LEVOMENOL 0.07 g/15 mL
INACTIVE INGREDIENTS: SUNFLOWER OIL; ADANSONIA DIGITATA SEED

ACTIVE INGREDIENT

Active ingredients: BISABOLOL 0.50%

INACTIVE INGREDIENT

Inactive ingredients: Helianthus Annuus (Sunflower) Seed Oil, Adansonia Digitata Seed Oil, Camellia Japonica Seed Oil, Caprylic/Capric Triglyceride, Oleic/Linoleic/Linolenic Polyglycerides, Pelargonium Graveolens Flower Oil, Citrus Aurantium Dulcis (Orange) Peel Oil, Boswellia Carterii Oil, Salvia Sclarea (Clary) Oil, Vetiveria Zizanoides Root Oil, Amyris Balsamifera Bark Oil, Melaleuca Alternifolia (Tea Tree) Leaf Oil, Daucus Carota Sativa (Carrot) Seed Oil, Rose Flower Oil, Camellia Oleifera Seed Oil, Rosa Canina Fruit Oil, Simmondsia Chinensis (Jojoba) Seed Oil, Hydrolyzed Vegetable Protein, Adansonia Digitata Fruit Extract, Glyceryl Caprylate, Tocopherol, Water, Maltodextrin, Saccharide Hydrolysate, Butylene Glycol, 1,2-Hexanediol, Hyaluronic Acid, Ethylhexylglycerin, Hydrolyzed Hyaluronic Acid, Sodium Hyaluronate, Phenoxyethanol

PURPOSE

Purpose: Skin Brightening

WARNINGS

Warnings: For external use only. Avoid contact with eyes. Discontinue use if signs of irritation or rashes appear. Replace the cap after use.

KEEP OUT OF REACH OF CHILDREN

Uses

Uses: Pump 2 ~3 drops of oil serum and gently spread over the entire face. Then cover your face with both hands for absorption.

Directions

Directions: 150000ppm of Adansonia Digitata Seed Oil with rich botanical oil quickly absorbs into skin to form a moisturizing barrier on dry skin and keeps it moisturized and hydrated. Moreover, it helps deliver a healthy skin condition and beauty. This whitening product contains Alpha-bisabolol ingredients to help brighten and purify skin. (Very effective simply by using 2 drops before makeup; depending on your skin’s dryness, you can use it by mixing with essence or cream.)